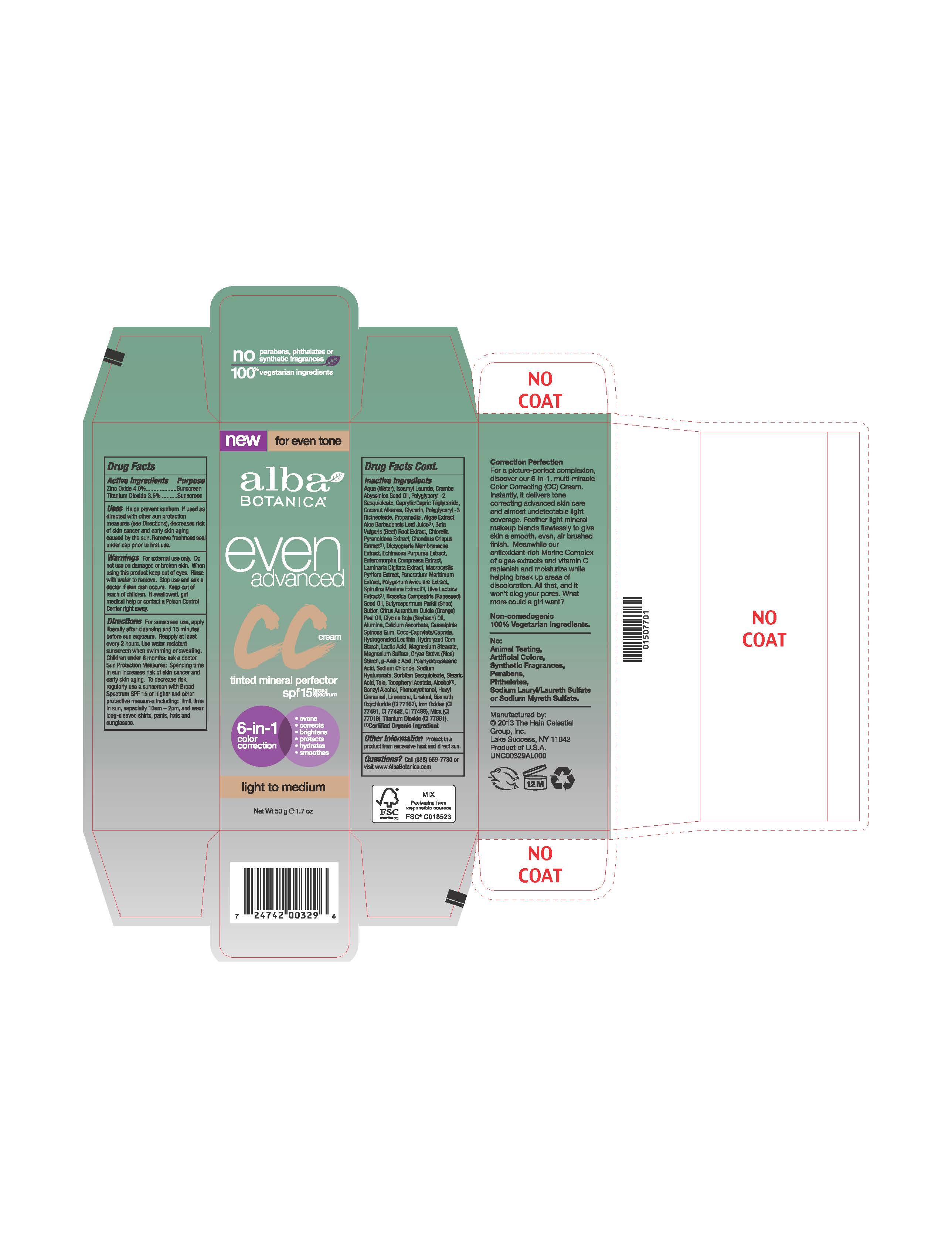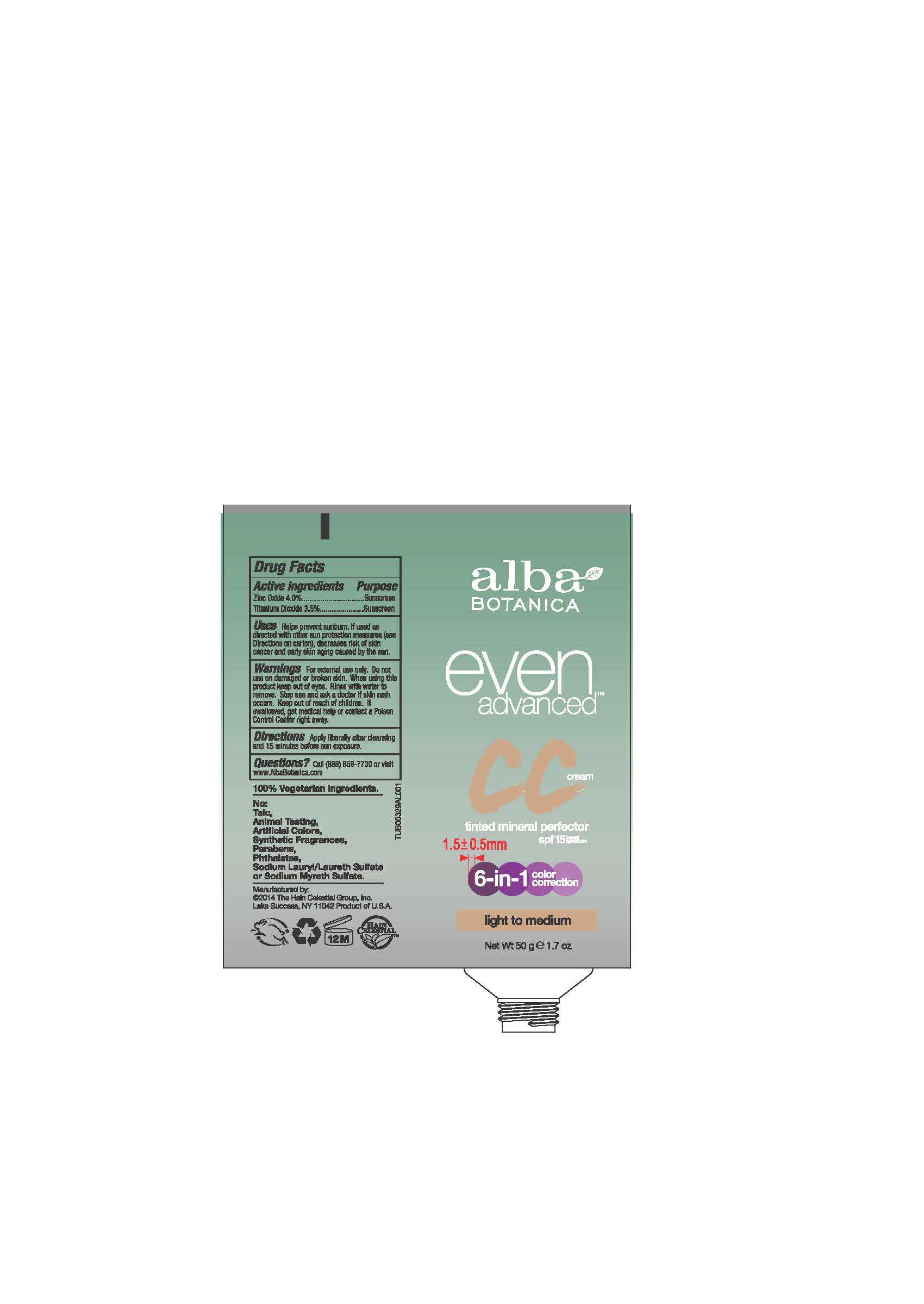 DRUG LABEL: Alba Even Advanced Mineral CC Cream Light to Medium SPF15
NDC: 61995-2032 | Form: CREAM
Manufacturer: The Hain Celestial Group, Inc.
Category: otc | Type: HUMAN OTC DRUG LABEL
Date: 20141024

ACTIVE INGREDIENTS: TITANIUM DIOXIDE 3.5 g/100 g; ZINC OXIDE 4 g/100 g
INACTIVE INGREDIENTS: STARCH, CORN; MAGNESIUM STEARATE; STARCH, RICE; SILICON DIOXIDE; HYALURONATE SODIUM; BISMUTH OXYCHLORIDE; SEAWEED; ULVA COMPRESSA; LAMINARIA DIGITATA; JOJOBA OIL, RANDOMIZED; PROPANEDIOL; BETA VULGARIS; CHLORELLA PYRENOIDOSA; CHONDRUS CRISPUS CARRAGEENAN; NARCISSUS TAZETTA BULB; SPIRULINA MAXIMA; ORANGE OIL; SOYBEAN OIL; CALCIUM ASCORBATE; CAESALPINIA SPINOSA RESIN; LACTIC ACID; ANISE; FERRIC OXIDE RED; MICA; ALCOHOL; BENZYL ALCOHOL; PHENOXYETHANOL; ALOE VERA LEAF; ISOAMYL LAURATE; COCONUT ALKANES; GLYCERIN; POLYGLYCERYL-3 RICINOLEATE; CRAMBE HISPANICA SUBSP. ABYSSINICA SEED OIL; WATER; SHEA BUTTER; BRASSICA RAPA SUBSP. OLEIFERA OIL; ALUMINUM OXIDE; COCO-CAPRYLATE/CAPRATE; MAGNESIUM SULFATE; SODIUM CHLORIDE; SORBITAN SESQUIOLEATE; STEARIC ACID; ECHINACEA PURPUREA ROOT; POLYHYDROXYSTEARIC ACID (2300 MW); MEDIUM-CHAIN TRIGLYCERIDES; .ALPHA.-TOCOPHEROL ACETATE; POLYGONUM AVICULARE TOP; ULVA LACTUCA; DICTYOPTERIS POLYPODIOIDES; MACROCYSTIS PYRIFERA

Active Ingredient

Zinc Oxide 4.0%

Titanium Dioxide 3.5%

DOSAGE AND ADMINISTRATION

Cream.For sunscreen use apply liberallyafter cleansing and 15 minutes before sun exposure. Reapply at least every 2 hours. Use water resistant sunscreen when swimming or sweating

PURPOSE

Sunscreen

WARNINGS

For external use only. Do not use on damaged or broken skin. When using this product keep out of eyes. Rinse with water to remove. Stop use and ask a doctor if skin rash occurs.

Keep out of reach of children. If swallowed get medical help or contact Poison Center right away.

INACTIVE INGREDIENT

Water, Caprylic Capric Triglyceride, Isoamyl Laurate, Coconut Alkanes,Polyglyceryl-2 Sesquioleate, Glycerin, Polyglyceryl-3 Ricinoleate, Crambe Abyssinica Seed Oil, Aloe Barbadensis Leaf Juice(1), Polyhydroxystearic Acid, Echinacea Purpurea Extract, Polygonum Aviculare Extract, Tocopheryl Acetate, Butyrospermum Parkii (Shea) Butter,Propanediol, Algae Extract, Beta Vulgaris (Beet)Root Extract, Chlorella Pyrenoidosa Extract, Dictyopteris Membranacea Extract, Chondrus Crispus Extract, Enteromorpha Compressa Extract, Laminaria Digitata Extract, Macrocystis Pyrifera Extract, Pancratium Maritimum Extract, Spirulina Maxima Extract, Ulva Lactuca Extract, Citrus Aurantium Dulcis (Orange) Peel Oil, Glycine Soja (Soybean) Oil, Brassica Campestris (Rapeseed) Seed Oil, Alumina, Calcium Ascorbate, Caesalpinia Spinosa Gum, Hydrolyzed Corn Starch, Jojoba Esters, Lactic Acid, Magnesium Stearate, Coco-Caprylate/Caprate, Magnesium Sulfate, Magnesium Stearate, Oryza Sativa (Rice) Starch, p-Anisic Acid, Silica, Sodium Chloride,Sodium Hyaluronate, Sorbitan Sesquioleate, Stearic Acid, Alcohol (1), Benzyl Alcohol, Phenoxyethanol, Bismuth Oxychloride, Iron Oxides, Mica.

(1) Certified Organicf Ingredient

INDICATIONS AND USAGE

Helps prevents sunburns. If uses as directed with other sun protection measures, decreases risk of skin cancer and early skin aging caused by sun exposure. Skin Protection Measures: Spending time in the sun increases your risk of skin cancer and early skin aging. To decrease risk, regularly use sunscreen with Broad Spectrum SPF 15 or higher and other protective measures including: limit time in sun, especially from10am to 2pm, and wear long sleeved shirts, pants, hats and sunglases.